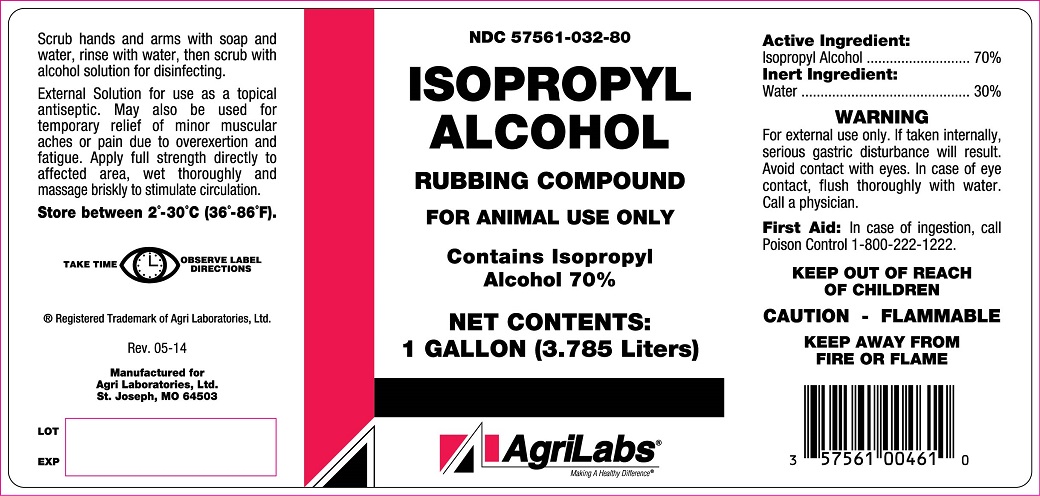 DRUG LABEL: ISOPROPYL ALCOHOL
NDC: 57561-032 | Form: LIQUID
Manufacturer: Agri Laboratories, Inc.
Category: animal | Type: OTC ANIMAL DRUG LABEL
Date: 20141002

ACTIVE INGREDIENTS: ISOPROPYL ALCOHOL 70 L/100 L
INACTIVE INGREDIENTS: WATER 30 L/100 L

ISOPROPYL ALCOHOL

DESCRIPTION

RUBBING COMPOUND

FOR ANIMAL USE ONLY

Contains Isopropyl Alcohol 70%

Scrub hands and arms with soap and water, rinse with water, then scrub with alcohol solution for disinfecting.

External Solution for use as a topical antiseptic. May also be used for temporary relief of minor muscular aches or pain due to overexertion and fatigue. Apply full strength directly to affected area, wet thoroughly and massage briskly to stimulate circulation.

TAKE TIME OBSERVE LABEL DIRECTIONS

STORAGE AND HANDLING

Store between 2o-30oC (36o-86 oF).

DOSAGE FORMS AND STRENGTHS

Active Ingredients
Isopropyl Alcohol ............................. 70%

Inert Ingredients
Water ............................................. 30%

WARNING

For external use only. If taken internally serious gastric disturbance will result.

Avoid contact with eyes. In case of eye contact, flush thoroughly with water. Call a physician.

First Aid
In case of ingestion, call Poison Control 1-800-222-1222.

KEEP OUT OF REACH OF CHILDREN

CAUTION - FLAMMABLE

KEEP AWAY FROM FIRE OR FLAME